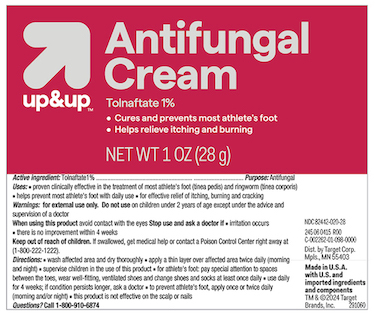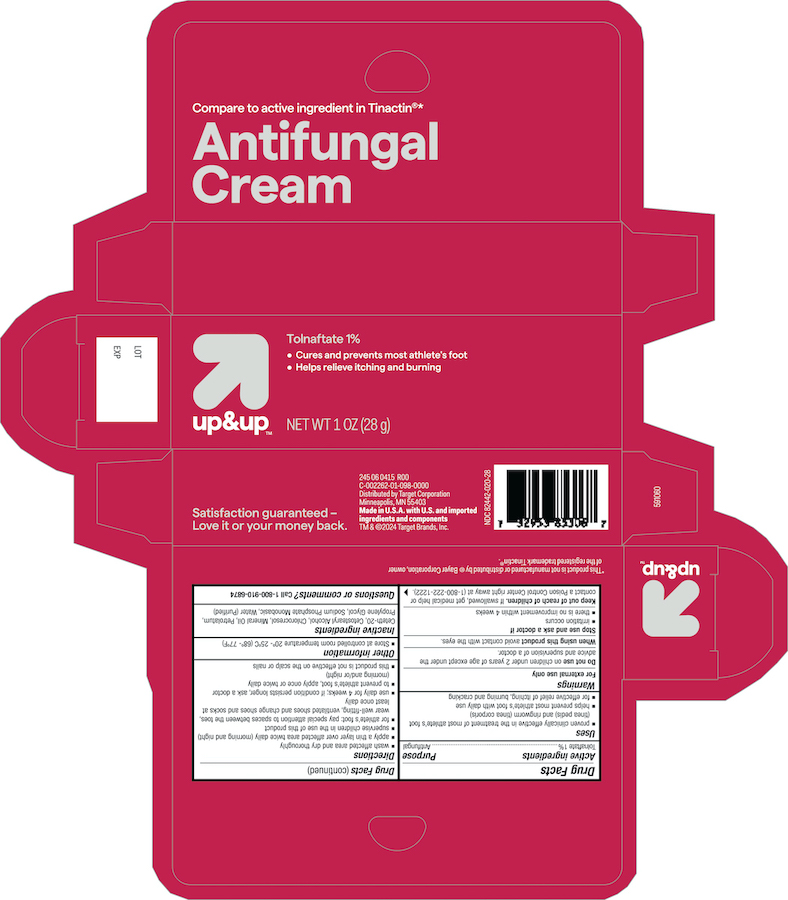 DRUG LABEL: Up and Up Antifungal
NDC: 82442-020 | Form: CREAM
Manufacturer: Target Corporation
Category: otc | Type: HUMAN OTC DRUG LABEL
Date: 20240508

ACTIVE INGREDIENTS: Tolnaftate 10 mg/1 g
INACTIVE INGREDIENTS: CETETH-20; CETOSTEARYL ALCOHOL; CHLOROCRESOL; MINERAL OIL; PETROLATUM; PROPYLENE GLYCOL; SODIUM PHOSPHATE, MONOBASIC, ANHYDROUS; WATER

Up and Up Antifungal Cream

Active ingredient

Tolnaftate 1%

Purpose

Antifungal

Uses

- for effective treatment of most athlete's foot (tinea pedis), jock itch (tinea cruris) and ringworm (tinea corporis)
- for effective relief of itchy, scaly skin between the toes
- clears up most athlete's foot infection and with daily use helps keep it from coming back

Warnings

For external use only

Do not use

- on children under 2 years of age unless directed by a doctor

When using this product avoid contact with eyes

Stop use and ask a doctor if

- irritation occurs or if there is no improvement within 4 weeks (for athlete's foot and ringworm)
- irritation occurs or if there is no improvement within 2 weeks (for jock itch)

Keep this and all drugs out of the reach of children.

In case of accidental ingestion, seek professional assistance or contact a Poison Control Center immediately.

Directions

- clean the affected area and dry thoroughly
- apply a thin layer of the product over the affected area twice daily (morning and night) or as directed by a doctor
- supervise children in the use of this product

For athlete's foot

- use daily for 4 weeks. If condition persists longer, consult a doctor
- pay special attention to the spaces between the toes
- wear well fitting ventilated shoes
- change shoes and socks at least once daily

For ringworm, use daily for 4 weeks. If condition persists longer, consult a doctor.
For jock itch, use daily for 2 weeks. If condition persists longer, consult a doctor.
This product is not effective on the scalp or nails.

Other information

store at controlled room temperature 20° -25°C (68-77°F)

Inactive ingredients

Ceteth-20, Cetostearyl Alcohol, Chlorocresol, Mineral Oil, Petrolatum , Propylene Glycol, Sodium Phosphate Monobasic, Water (Purified)

Principal display panel

Up &Up NDC 82442-020-28

Antifungal Cream

Tolnaftate 1%

NET WT 1 OZ (28g)